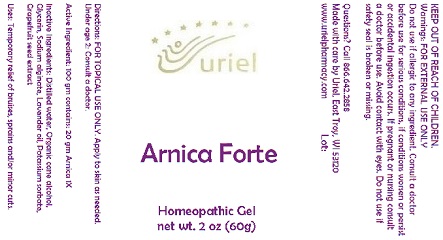 DRUG LABEL: Arnica Forte
NDC: 48951-1146 | Form: GEL
Manufacturer: Uriel Pharmacy Inc.
Category: homeopathic | Type: HUMAN OTC DRUG LABEL
Date: 20170720

ACTIVE INGREDIENTS: ARNICA MONTANA FLOWER 1 [hp_X]/1 g
INACTIVE INGREDIENTS: WATER; ALCOHOL; GLYCERIN; SODIUM ALGINATE; LAVENDER OIL; POTASSIUM SORBATE; CITRUS PARADISI SEED

Arnica Forte

INDICATIONS AND USAGE

Directions: FOR TOPICAL USE ONLY.

DOSAGE AND ADMINISTRATION

Apply to skin as needed. Under age 2: Consult a doctor.

Active Ingredient: 100 gm contains: 20 gm Arnica 1X

INACTIVE INGREDIENT

Inactive Ingredients: Distilled water, Organic cane alcohol, Glycerin, Sodium alginate, Lavender oil, Potassium sorbate, Grapefruit seed extract

PURPOSE

Uses: Temporary relief of bruises, sprains and/or minor cuts.

KEEP OUT OF REACH OF CHILDREN.

WARNINGS

Warnings: FOR EXTERNAL USE ONLY Do not use if allergic to any ingredient. Consult a doctor before use for serious conditions, if conditions worsen or persist or accidental ingestion occurs. If pregnant or nursing consult a doctor before use. Avoid contact with eyes. Do not use if safety seal is broken or missing.

QUESTIONS

Questions? Call 866.642.2858 Made with care by Uriel, East Troy, WI 53120 www.urielpharmacy.com